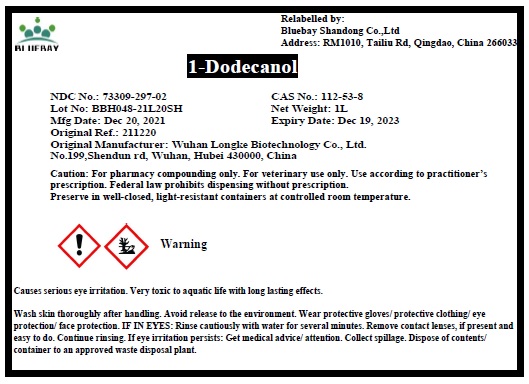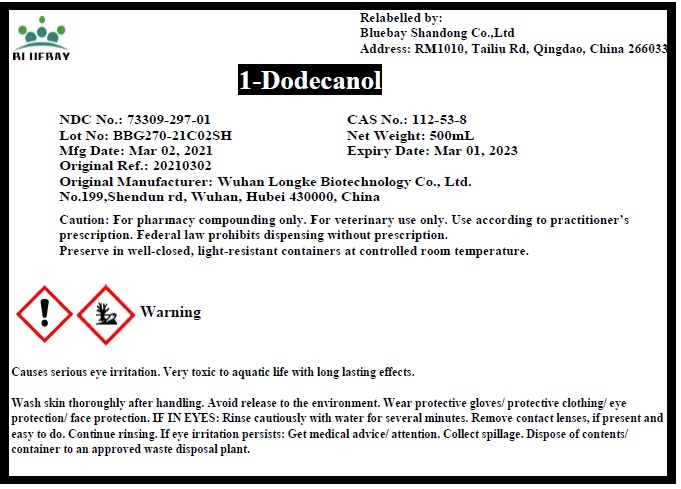 DRUG LABEL: 1-Dodecanol
NDC: 73309-297 | Form: LIQUID
Manufacturer: BLUEBAY SHANDONG CO.,LTD
Category: other | Type: BULK INGREDIENT - ANIMAL DRUG
Date: 20220307

ACTIVE INGREDIENTS: LAURYL ALCOHOL 1 mL/1 mL

1-Dodecanol